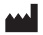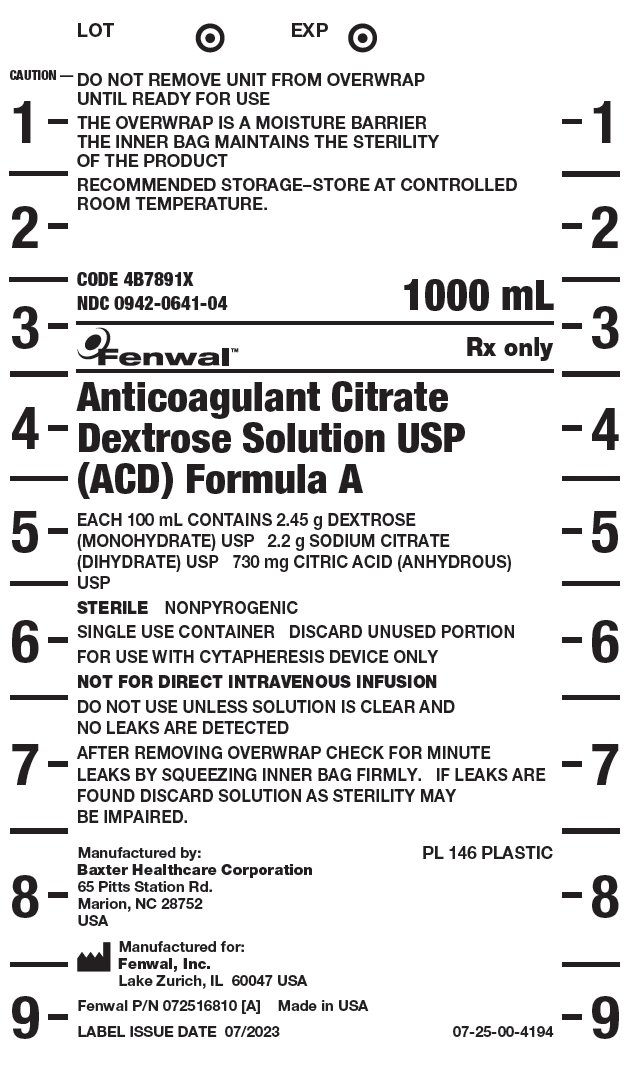 DRUG LABEL: ACD-A
NDC: 0942-0641 | Form: SOLUTION
Manufacturer: Fenwal, Inc.
Category: prescription | Type: HUMAN PRESCRIPTION DRUG LABEL
Date: 20251125

ACTIVE INGREDIENTS: Dextrose Monohydrate 24.5 g/1000 mL; SODIUM CITRATE, UNSPECIFIED FORM 22 g/1000 mL; Anhydrous Citric Acid 7.3 g/1000 mL
INACTIVE INGREDIENTS: Water

Anticoagulant Citrate Dextrose Solution USP (ACD) Formula A

CAUTION —

DO NOT REMOVE UNIT FROM OVERWRAP UNTIL READY FOR USE

THE OVERWRAP IS A MOISTURE BARRIER
THE INNER BAG MAINTAINS THE STERILITY OF THE PRODUCT

RECOMMENDED STORAGE–STORE AT CONTROLLED ROOM TEMPERATURE.

CODE 4B7891X
NDC 0942-0641-04

1000 mL

Fenwal™

Rx only

Anticoagulant Citrate Dextrose Solution USP (ACD) Formula A

EACH 100 mL CONTAINS 2.45 g DEXTROSE (MONOHYDRATE) USP 2.2 g SODIUM CITRATE (DIHYDRATE) USP 730 mg CITRIC ACID (ANHYDROUS) USP

STERILE

NONPYROGENIC

SINGLE USE CONTAINER

DISCARD UNUSED PORTION

FOR USE WITH CYTAPHERESIS DEVICE ONLY

NOT FOR DIRECT INTRAVENOUS INFUSION

DO NOT USE UNLESS SOLUTION IS CLEAR AND NO LEAKS ARE DETECTED

AFTER REMOVING OVERWRAP CHECK FOR MINUTE LEAKS BY SQUEEZING INNER BAG FIRMLY. IF LEAKS ARE FOUND DISCARD SOLUTION AS STERILITY MAY BE IMPAIRED

Rx only

PL 146 PLASTIC

Manufactured by:
Baxter Healthcare Corporation
65 Pitts Station Rd.

Marion, NC 28752

USA

Manufactured for:
Fenwal, Inc.
Lake Zurich, IL 60047 USA

Fenwal P/N072516810 Made in USA

LABEL ISSUE DATE 07/2023

07-25-00-4194